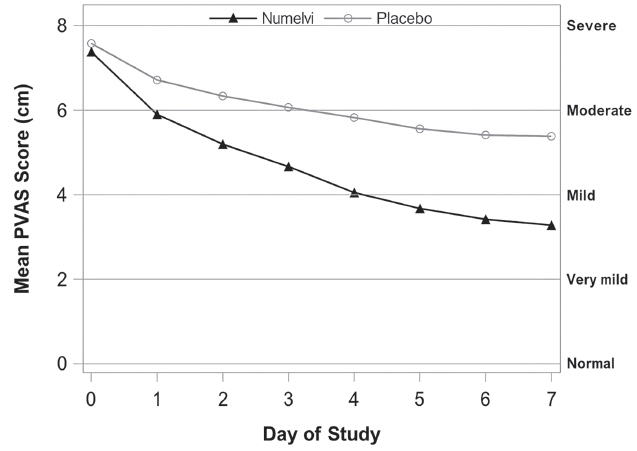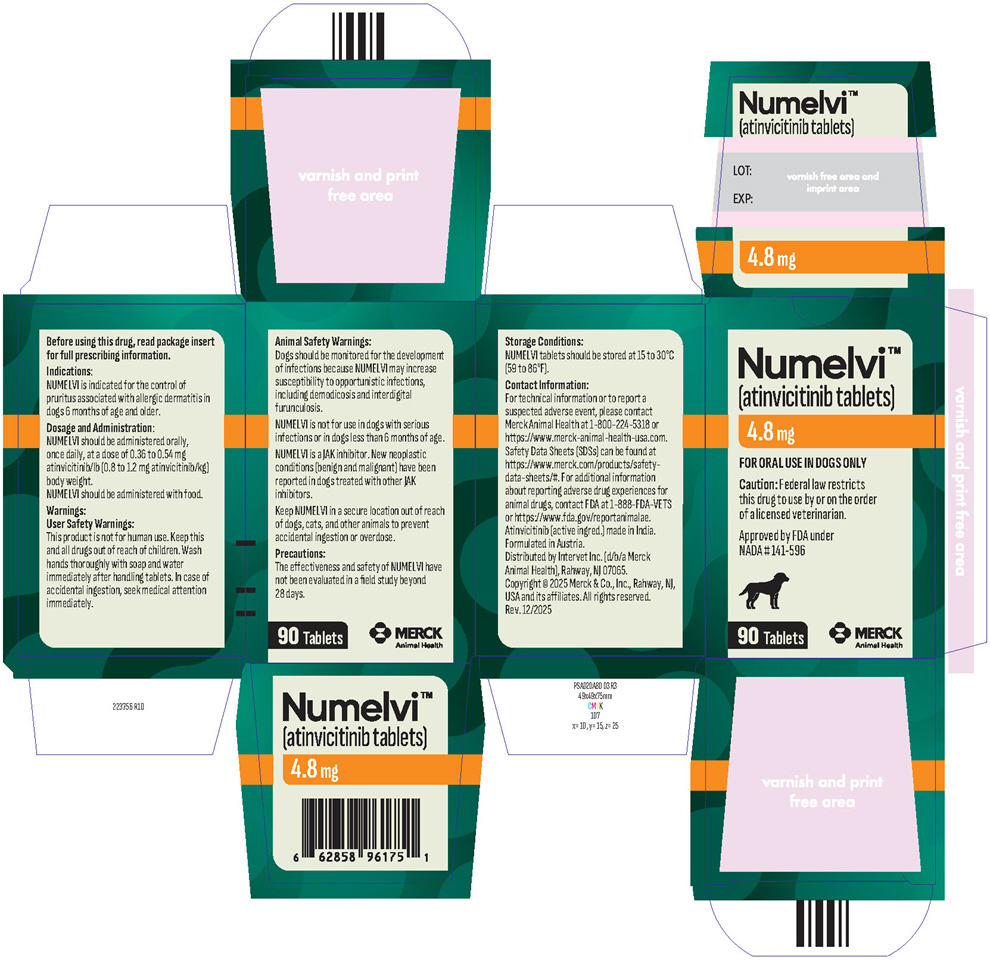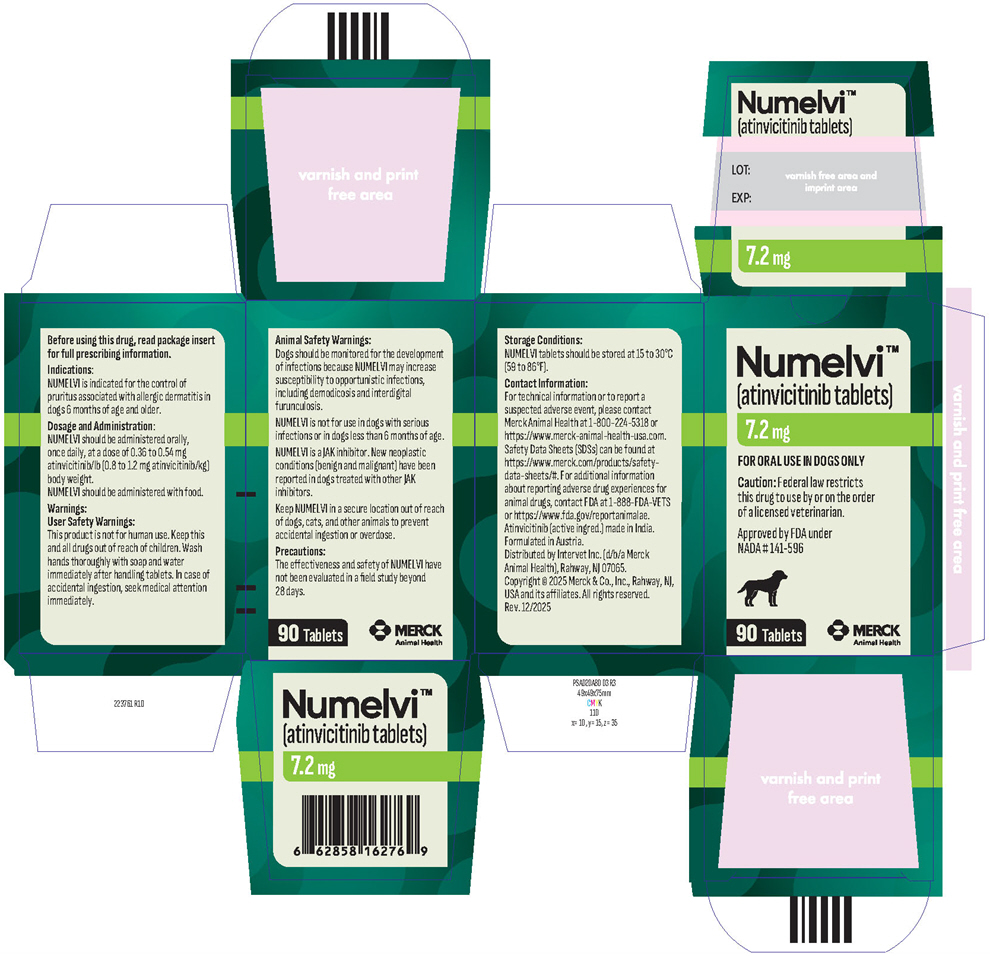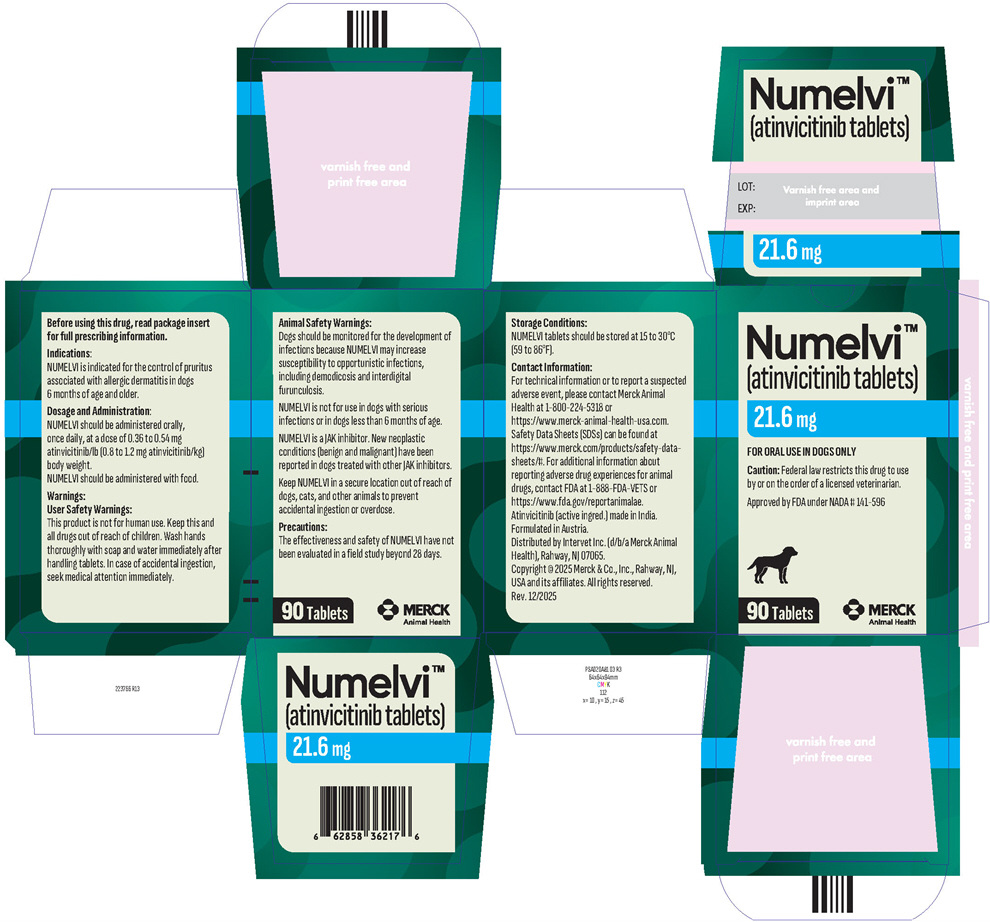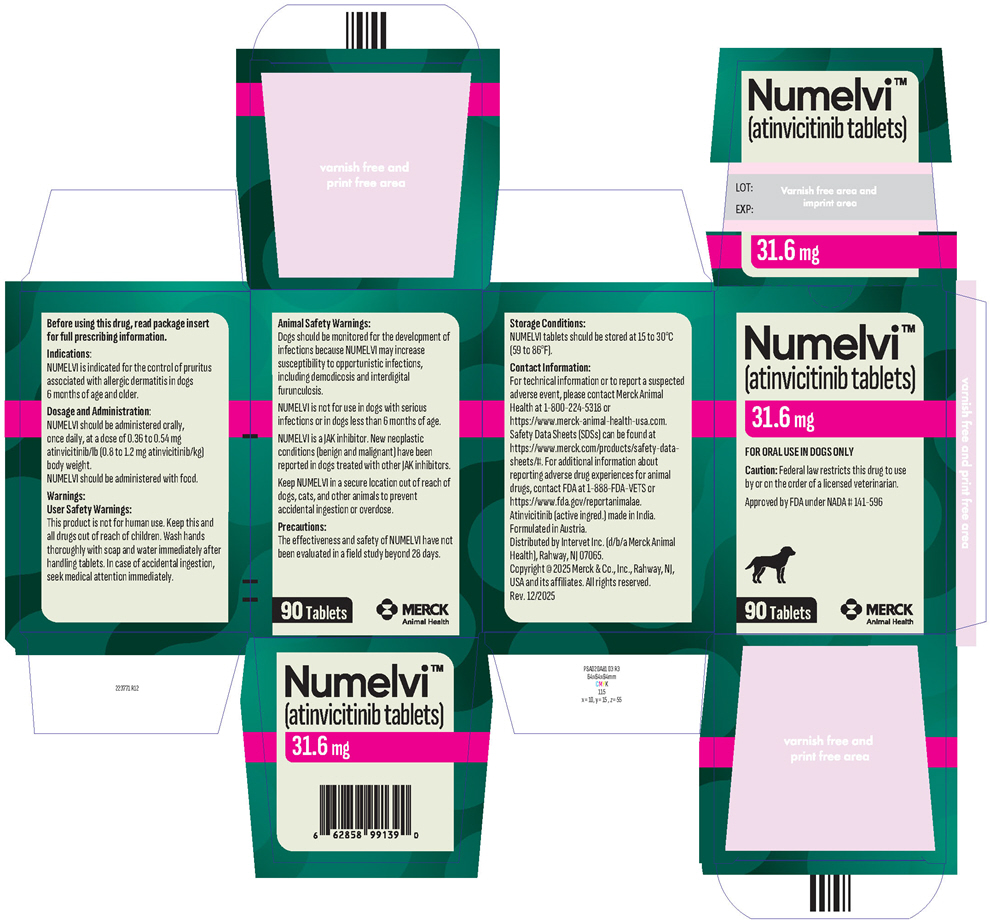 DRUG LABEL: Numelvi
NDC: 0061-1434 | Form: TABLET
Manufacturer: Merck Sharp & Dohme Corp.
Category: animal | Type: PRESCRIPTION ANIMAL DRUG LABEL
Date: 20260226

ACTIVE INGREDIENTS: ATINVICITINIB 4.8 mg/1 1

Numelvi™
(atinvicitinib tablets)

Immunomodulator
223751 R10

For oral use in dogs only

WARNINGS

CAUTION: Federal law restricts this drug to use by or on the order of a licensed veterinarian.

DESCRIPTION:

The active ingredient in NUMELVI is atinvicitinib. Atinvicitinib is a synthetic selective Janus kinase (JAK) 1 inhibitor. The chemical (IUPAC) name of atinvicitinib is 1-[(3R,4S)-4-cyanooxan-3-yl]-3-[(2-fluoro-6-methoxypyridin-4-yl)amino]-1H-pyrazole-4-carboxamide.

INDICATIONS:

NUMELVI is indicated for the control of pruritus associated with allergic dermatitis in dogs 6 months of age and older.

DOSAGE AND ADMINISTRATION:

NUMELVI should be administered orally, once daily, at a dose of 0.36 to 0.54 mg atinvicitinib/lb (0.8 to 1.2 mg atinvicitinib/kg) body weight according to the Dosing Table below.

NUMELVI should be administered with food.

Dosing Table

Body Weight Ranges (lb) | Body Weight Ranges (kg) | Number of Tablets to be Administered
Body Weight Ranges (lb) | Body Weight Ranges (kg) | 4.8 mg tablets | 7.2 mg tablets | 21.6 mg tablets | 31.6 mg tablets
4.4 - 6.5 | 2 - 2.9 | 0.5
6.6 - 9.5 | 3 - 4.3 |  | 0.5
9.6 - 13.3 | 4.4 - 6 | 1
13.4 - 19.9 | 6.1 - 9 |  | 1
20 - 29.8 | 9.1 - 13.5 |  |  | 0.5
29.9 - 42.6 | 13.6 - 19.3 |  |  |  | 0.5
42.7 - 58.4 | 19.4 - 26.5 |  |  | 1
58.5 - 87 | 26.6 - 39.5 |  |  |  | 1
87.1 - 118.9 | 39.6 - 54 |  |  |  | 1.5
119 - 174.2 | 54.1 - 79 |  |  |  | 2
≥ 174.3 | ≥79.1 | Administer the appropriate combination of tablet strengths

WARNINGS:

User Safety Warnings:

This product is not for human use. Keep this and all drugs out of reach of children. Wash hands thoroughly with soap and water immediately after handling tablets. In case of accidental ingestion, seek medical attention immediately.

Animal Safety Warnings:

Dogs should be monitored for the development of infections because NUMELVI may increase susceptibility to opportunistic infections, including demodicosis and interdigital furunculosis (see Target Animal Safety).

NUMELVI is not for use in dogs with serious infections.

NUMELVI is a JAK inhibitor. New neoplastic conditions (benign and malignant) have been reported in dogs treated with other JAK inhibitors.

Consider the risks and benefits of treatment prior to initiating NUMELVI in dogs with a history of recurrent demodicosis.

NUMELVI modulates the immune system.

NUMELVI is not for use in dogs less than 6 months of age (see Target Animal Safety).

Keep NUMELVI in a secure location out of reach of dogs, cats, and other animals to prevent accidental ingestion or overdose.

PRECAUTIONS:

The effectiveness and safety of NUMELVI have not been evaluated in a field study beyond 28 days (see Adverse Reactions and Effectiveness).

The safe use of NUMELVI has not been evaluated in breeding, pregnant, or lactating dogs. Decreased mean testes weight was observed in a laboratory safety study (see Target Animal Safety).

The safe use of NUMELVI has not been evaluated in combination with glucocorticoids, cyclosporine, or other systemic immunosuppressive agents.

ADVERSE REACTIONS:

In a masked field study assessing effectiveness and safety of NUMELVI for the control of pruritus associated with allergic dermatitis in dogs, 144 NUMELVI-treated dogs and 144 placebo-treated dogs were evaluated for safety for up to 28 days. Adverse reactions seen during the field study are summarized in Table 1 below.

Table 1. Adverse Reactions through Day 28
Adverse Reaction | NUMELVI (N=144) Number of dogs (%) | Placebo (N=144) Number of dogs (%)
Vomiting or nausea | 10 (6.9%) | 6 (4.2%)
Otitis externa | 9 (6.3%) | 8 (5.6%)
Hematuria (without urinary tract infection) | 7 (4.9%) | 6 (4.2%)
Anorexia | 6 (4.2%) | 5 (3.5%)
Bacterial skin infection | 6 (4.2%) | 10 (6.9%)
Diarrhea | 6 (4.2%) | 15 (10.4%)
Crystalluria | 5 (3.5%) | 2 (1.4%)
Lethargy | 5 (3.5%) | 5 (3.5%)
Urinary tract infection | 5 (3.5%) | 5 (3.5%)
Upset stomach, including flatulence, retching, and bloating | 3 (2.1%) | 0
Neurological disorder (e.g., tremors, ataxia) | 2 (1.4%) | 1 (0.7%)
Ocular discharge | 2 (1.4%) | 1 (0.7%)
Coughing | 1 (0.7%) | 0
Granuloma | 1 (0.7%) | 0
Increased urination | 1 (0.7%) | 0

Abnormal hematology results likely related to NUMELVI administration included leukopenia, neutropenia, eosinopenia, monocytopenia, and lymphocytosis.

Abnormal serum chemistry results likely related to NUMELVI administration included increased alanine aminotransferase (ALT), aspartate aminotransferase (AST), and symmetric dimethylarginine (SDMA), and hypercholesterolemia.

Three NUMELVI-treated dogs withdrew from the study early due to an adverse reaction, two of which were considered likely related to NUMELVI treatment (i.e., diarrhea). Two placebo-treated dogs also withdrew from the study early due to an adverse reaction (i.e., diarrhea).

CONTACT INFORMATION:

For technical information or to report a suspected adverse event, please contact Merck Animal Health at 1-800-224-5318 or https://www.merck-animal-health-usa.com. Safety Data Sheets (SDSs) can be found at https://www.merck.com/products/safety-data-sheets/#.

For additional information about reporting adverse drug experiences for animal drugs, contact FDA at 1-888-FDA-VETS or https://www.fda.gov/reportanimalae.

CLINICAL PHARMACOLOGY:

Mechanism of Action

Atinvicitinib is a Janus kinase (JAK) inhibitor. It inhibits the function of a variety of pruritogenic, pro-inflammatory and allergy related cytokines that are dependent upon JAK enzymes. Atinvicitinib is more selective for JAK1 compared to JAK2, JAK3, and tyrosine kinase 2 (TYK2). Atinvicitinib is not a corticosteroid or an antihistamine.

Pharmacokinetics

In a laboratory margin of safety study in healthy 6-month-old dogs (see Target Animal Safety), after repeat daily oral administration of atinvicitinib at 1.2 mg/kg for 6 months, the atinvicitinib mean (coefficient of variation % [CV%]) maximum concentration (Cmax) was 214 ng/mL (42%) with a median Tmax (time to Cmax) of 2 (range 1-6) hours. The mean area under the curve from the time of dosing to the last quantifiable plasma concentration (AUClast) and half-life were 888 h*ng/mL (27%) and 2.3 hours (27%), respectively. Minimal accumulation was observed between Days 1 and 182 with geometric mean accumulation ratios for Cmax and AUClast of 1.0 and 1.2. AUClast and Cmax increased in a linear but less than proportional manner where a 5-fold increase in dose resulted in a 4.5-fold (95% confidence interval [CI]: 3.6-5.3) and 3.7-fold (95% CI: 3.1-4.2) increase in AUClast and Cmax , respectively.

Following a single oral or intravenous administration of atinvicitinib, the geometric mean oral bioavailability based on AUClast was 45.5%.

The mean systemic clearance following intravenous administration is 1074 mL/h/kg with a harmonic mean terminal half-life of 1.1 hours and a mean volume of distribution of 1651 mL/kg. Following a single oral administration of atinvicitinib at 1.2 mg/kg, Cmax and AUClast were 280% and 120% higher, respectively, in the fed state as compared to the fasted state (n=16). Atinvicitinib was found to be mainly excreted in the feces while urinary elimination was a minor route of excretion. Atinvicitinib has moderate protein binding with 82.3% bound in fortified canine plasma at a concentration of 1802 ng/mL (5 μM).

EFFECTIVENESS:

A masked, 28-day, placebo-controlled study was conducted at 26 veterinary clinics in the US, enrolling 288 client-owned dogs diagnosed with allergic dermatitis and having at least moderate pruritus. The allergic dermatitis was attributed to one or more of the following conditions (in the order of frequency): atopic dermatitis, unspecified allergic dermatitis, food hypersensitivity, flea allergy dermatitis, and contact dermatitis. Dogs were randomized to once daily treatment with NUMELVI at 0.8 - 1.2 mg/kg or placebo, at a ratio of 1:1 respectively. Other medications that could affect the evaluation of effectiveness were not allowed during the study, such as corticosteroids, antihistamines, and cyclosporine. Treatment success for each dog was defined as a ≥ 50% reduction from baseline in owner-assessed pruritus scores on the Pruritus Visual Analog Scale (PVAS) on at least 5 out of the first 7 days of treatment. The proportion of dogs in the NUMELVI group that were treatment successes was greater than and significantly different compared to the placebo group on Day 7 (Table 2, below).

Table 2. Estimated Proportion of Dogs Achieving Treatment Success
Treatment Group | Estimated Proportion of Success [Based on back-transformed least squares means.]
NUMELVI (N = 125) | 0.23
Placebo (N = 125) | 0.07 [Placebo vs. NUMELVI p = 0.0128]
N = number of dogs

Mean owner-assessed PVAS scores were lower in the NUMELVI group after Day 0 (Figure 1, below).

Figure 1: Mean owner-assessed PVAS Scores by Treatment for Days 0-7

Veterinarians used a Dermatitis Visual Analog Scale (DVAS) to assess each dog's dermatitis. Veterinarian-assessed DVAS scores were lower for the NUMELVI group compared to the placebo group at all time points through Day 28.

TARGET ANIMAL SAFETY:

Margin of Safety Study

NUMELVI was administered orally to 24 healthy, 6-month-old Beagle dogs at 1X, 3X, and 5X (8 dogs per group) the maximum labeled dose of 1.2 mg/kg once daily for 6 months. The 8 dogs in the control group were sham dosed. Dogs were dosed in the fed state. One dog in the 5X group developed progressive alopecia, fever, lethargy, generalized lymphadenitis, interdigital furunculosis (cysts), interdigital swellings, and pustules on the border of the oral cavity. The dog had a declining clinical condition under continued treatment with NUMELVI and was euthanized on Day 175. The lesions were histologically consistent with generalized demodicosis including marked, chronic, active dermal inflammation, and minimal, multifocal, neutrophilic infiltration in the mandibular lymph node and were considered due to NUMELVI-induced immunosuppression. The dog demonstrated greater systemic exposure to NUMELVI (higher Cmax and AUClast values) compared to other dogs in the 5X group. One dog in the 3X group developed a single interdigital cyst with no Demodex canis mites identified in the hair follicles. Male dogs in the NUMELVI treatment groups had decreased mean testes weight compared to the control dogs. Microscopic pathology findings in one 1X dog with pre-existing unilateral cryptorchidism and one 3X dog included unilateral, focal, minimal testicular tubular hypoplasia. There were no NUMELVI-related effects on clinical pathology.

Vaccine Response Study

NUMELVI was administered orally to 10 healthy, 6-month-old, vaccine naïve Beagle dogs at 3X the maximum labeled dose of 1.2 mg/kg once daily for 84 days. The dogs in the control group (10) received placebo tablets. All dogs were dosed in the fed state. After the last dose on Day 84, all dogs were observed for an additional 84 days. All dogs received a multivalent modified live canine adenovirus type-2 (CAV), canine distemper virus (CDV), canine parvovirus (CPV) vaccination and a killed rabies virus (RV) vaccination on Day 28. An additional multivalent modified live CAV, CDV, CPV vaccination was administered on Day 56. All dogs in the NUMELVI treatment group demonstrated an adequate serological immune response to the modified live CAV, CDV, CPV, and killed RV vaccination on Day 84. There were no NUMELVI-related adverse clinical effects.

STORAGE CONDITIONS:

NUMELVI tablets should be stored at 15 to 30°C (59 to 86°F).

HOW SUPPLIED:

NUMELVI (atinvicitinib tablets) is available in scored tablets in four strengths: 4.8 mg, 7.2 mg, 21.6 mg, and 31.6 mg per tablet. Each tablet strength is available in 30 and 90 count bottles. Each tablet is marked with an S, M, L, or XL that correspond to the different tablet strengths.

Approved by FDA under NADA # 141-596

Formulated in Austria.
Distributed by Intervet Inc. (d/b/a Merck Animal Health), Rahway, NJ 07065.
Copyright © 2025 Merck & Co., Inc., Rahway, NJ, USA and its affiliates.
All rights reserved.
Rev. 12/2025

MERCK
Animal Health

PRINCIPAL DISPLAY PANEL - 4.8 mg Bottle Carton

Numelvi™
(atinvicitinib tablets)

4.8 mg

FOR ORAL USE IN DOGS ONLY

Caution: Federal law restricts
this drug to use by or on the order
of a licensed veterinarian.

Approved by FDA under
NADA # 141-596

90 Tablets

MERCK
Animal Health

PRINCIPAL DISPLAY PANEL - 7.2 mg Bottle Carton

Numelvi™
(atinvicitinib tablets)

7.2 mg

FOR ORAL USE IN DOGS ONLY

Caution: Federal law restricts
this drug to use by or on the order
of a licensed veterinarian.

Approved by FDA under
NADA # 141-596

90 Tablets

MERCK
Animal Health

PRINCIPAL DISPLAY PANEL - 21.6 mg Bottle Carton

Numelvi™
(atinvicitinib tablets)

21.6 mg

FOR ORAL USE IN DOGS ONLY

Caution: Federal law restricts this drug to use
by or on the order of a licensed veterinarian.

Approved by FDA under NADA # 141-596

90 Tablets

MERCK
Animal Health

PRINCIPAL DISPLAY PANEL - 31.6 mg Bottle Carton

Numelvi™
(atinvicitinib tablets)

31.6 mg

FOR ORAL USE IN DOGS ONLY

Caution: Federal law restricts this drug to use
by or on the order of a licensed veterinarian.

Approved by FDA under NADA # 141-596

90 Tablets

MERCK
Animal Health